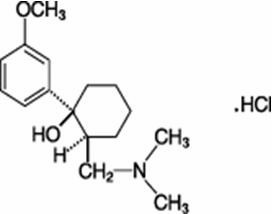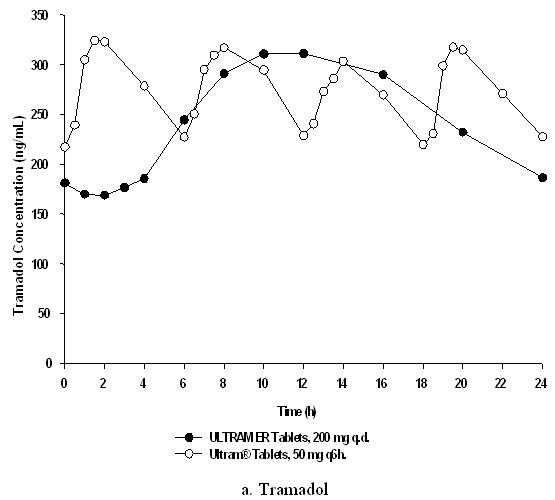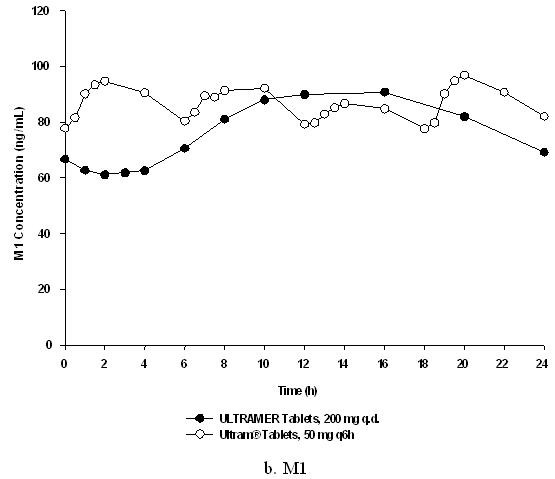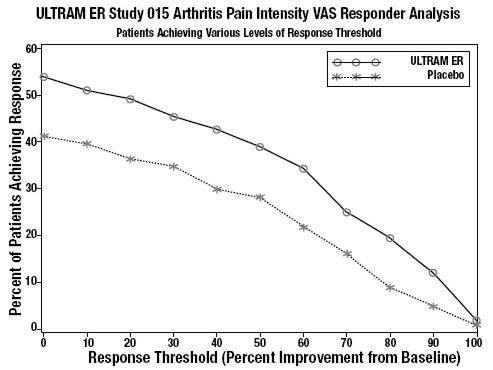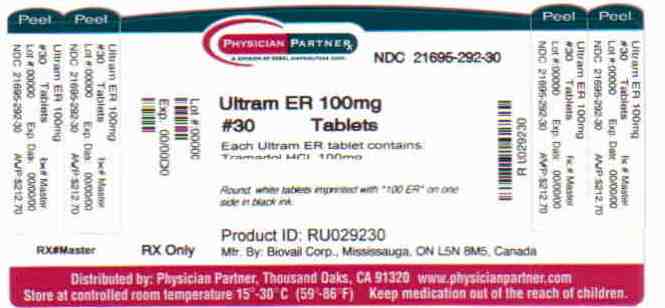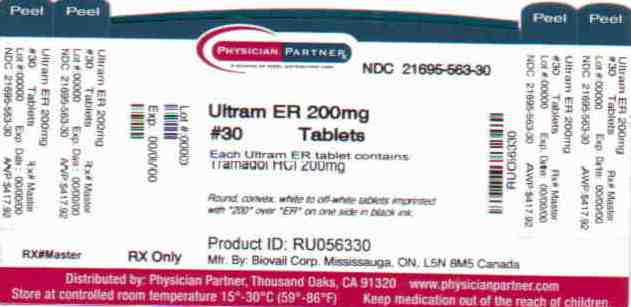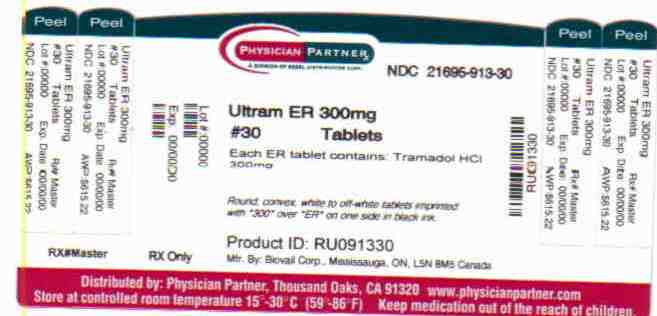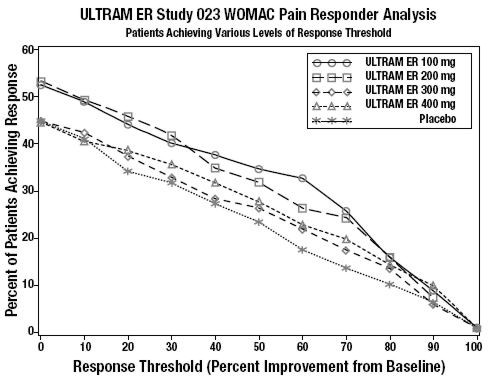 DRUG LABEL: ULTRAM ER
NDC: 21695-292 | Form: TABLET, EXTENDED RELEASE
Manufacturer: Rebel Distributors Corp
Category: prescription | Type: HUMAN PRESCRIPTION DRUG LABEL
Date: 20101201

ACTIVE INGREDIENTS: tramadol hydrochloride 100 mg/1 1
INACTIVE INGREDIENTS: ETHYLCELLULOSES; dibutyl sebacate; 1-VINYL-2-PYRROLIDONE; SODIUM STEARYL FUMARATE; SILICON DIOXIDE; POLYVINYL ALCOHOL

ULTRAM® ER
(tramadol HCl) Extended-Release Tablets

Rx only

Prescribing Information

DESCRIPTION

ULTRAM® ER (tramadol hydrochloride) is a centrally acting synthetic analgesic in an extended-release formulation. The chemical name is (±) cis-2-[(dimethylamino)methyl]-1-(3-methoxyphenyl) cyclohexanol hydrochloride. Its structural formula is:

Figure 1

The molecular weight of tramadol HCl is 299.8. It is a white, bitter, crystalline and odorless powder that is readily soluble in water and ethanol and has a pKa of 9.41. The n-octanol/water log partition coefficient (logP) is 1.35 at pH 7. ULTRAM ER tablets contain 100, 200 or 300 mg of tramadol HCl in an extended-release formulation. The tablets are white to off-white in color and contain the inactive ingredients ethylcellulose, dibutyl sebacate, polyvinyl pyrrolidone, sodium stearyl fumarate, colloidal silicon dioxide, and polyvinyl alcohol.

CLINICAL PHARMACOLOGY

Mechanism of Action

ULTRAM ER is a centrally acting synthetic opioid analgesic. Although its mode of action is not completely understood, from animal tests, at least two complementary mechanisms appear applicable: binding of parent and M1 metabolite to µ-opioid receptors and weak inhibition of reuptake of norepinephrine and serotonin.

Opioid activity is due to both low affinity binding of the parent compound and higher affinity binding of the O-demethylated metabolite M1 to µ-opioid receptors. In animal models, M1 is up to 6 times more potent than tramadol in producing analgesia and 200 times more potent in µ-opioid binding. Tramadol-induced analgesia is only partially antagonized by the opiate antagonist naloxone in several animal tests. The relative contribution of both tramadol and M1 to human analgesia is dependent upon the plasma concentrations of each compound.

Tramadol has been shown to inhibit reuptake of norepinephrine and serotonin in vitro, as have some other opioid analgesics. These mechanisms may contribute independently to the overall analgesic profile of tramadol. The relationship between exposure of tramadol and M1 and efficacy has not been evaluated in the ULTRAM ER clinical studies.

Apart from analgesia, tramadol administration may produce a constellation of symptoms (including dizziness, somnolence, nausea, constipation, sweating and pruritus) similar to that of other opioids. In contrast to morphine, tramadol has not been shown to cause histamine release. At therapeutic doses, tramadol has no effect on heart rate, left-ventricular function or cardiac index. Orthostatic hypotension has been observed.

Pharmacokinetics

The analgesic activity of tramadol is due to both parent drug and the M1 metabolite. ULTRAM ER is administered as a racemate and both the [-] and [+] forms of both tramadol and M1 are detected in the circulation.

The pharmacokinetics of ULTRAM ER are approximately dose-proportional over a 100-400 mg dose range in healthy subjects. The observed tramadol AUC values for the 400-mg dose were 26% higher than predicted based on the AUC values for the 200-mg dose. The clinical significance of this finding has not been studied and is not known.

Absorption

In healthy subjects, the bioavailability of a ULTRAM ER 200 mg tablet relative to a 50 mg every six hours dosing regimen of the immediate-release dosage form (ULTRAM) was approximately 85-90%. Consistent with the extended-release nature of the formulation, there is a lag time in drug absorption following ULTRAM ER administration. The mean peak plasma concentrations of tramadol and M1 after administration of ULTRAM ER tablets to healthy volunteers are attained at about 12 h and 15 h, respectively, after dosing (see Table 1 and Figure 2). Following administration of the ULTRAM ER, steady-state plasma concentrations of both tramadol and M1 are achieved within four days with once daily dosing.

The mean (%CV) pharmacokinetic parameter values for ULTRAM ER 200 mg administered once daily and tramadol HCl immediate-release (ULTRAM) 50 mg administered every six hours are provided in Table 1.

Table 1.
Mean (%CV) Steady-State Pharmacokinetic Parameter Values (n=32)
 | Tramadol |  | M1 Metabolite
Pharma- cokinetic Parameter | ULTRAM ER 200-mg Tablet Once-Daily | ULTRAM 50-mg Tablet Every 6 Hours | ULTRAM ER 200-mg Tablet Once-Daily | ULTRAM 50-mg Tablet Every 6 Hours
AUC0-24 (ng∙h/mL) | 5975 (34) | 6613 (27) | 1890 (25) | 2095 (26)
Cmax (ng/mL) | 335 (35) | 383 (21) | 95 (24) | 104 (24)
Cmin (ng/mL) | 187 (37) | 228 (32) | 69 (30) | 82 (27)
Tmax (h) | 12 (27) | 1.5 (42) | 15 (27) | 1.9 (57)
% Fluctuation | 61 (57) | 59 (35) | 34 (72) | 26 (47)
AUC0-24: Area Under the Curve in a 24-hour dosing interval; Cmax: Peak Concentration in a 24-hour dosing interval;
Cmin: Trough Concentration in a 24-hour dosing interval; Tmax: Time to Peak Concentration

Figure 2: Mean Steady-State Tramadol (a) and M1 (b) Plasma Concentrations on Day 8 Post Dose after Administration of 200 mg ULTRAM ER Once-Daily and 50 mg ULTRAM Every 6 Hours.

Food Effects

After a single dose administration of 200 mg ULTRAM ER tablet with a high fat meal, the Cmax and AUC0-∞ of tramadol decreased 28% and 16%, respectively, compared to fasting conditions. Mean Tmax was increased by 3 hr (from 14 hr under fasting conditions to 17 hr under fed conditions). While ULTRAM ER may be taken without regard to food, it is recommended that it be taken in a consistent manner.

Distribution

The volume of distribution of tramadol was 2.6 and 2.9 liters/kg in male and female subjects, respectively, following a 100-mg intravenous dose. The binding of tramadol to human plasma proteins is approximately 20% and binding also appears to be independent of concentration up to 10 µg/mL. Saturation of plasma protein binding occurs only at concentrations outside the clinically relevant range.

Metabolism

Tramadol is extensively metabolized after oral administration. The major metabolic pathways appear to be N – (mediated by CYP3A4 and CYP2B6) and O – (mediated by CYP2D6) demethylation and glucuronidation or sulfation in the liver. One metabolite (O-desmethyl tramadol, denoted M1) is pharmacologically active in animal models. Formation of M1 is dependent on CYP2D6 and as such is subject to inhibition, which may affect the therapeutic response (see PRECAUTIONS, Drug Interactions).

Elimination

Tramadol is eliminated primarily through metabolism by the liver and the metabolites are eliminated primarily by the kidneys. Approximately 30% of the dose is excreted in the urine as unchanged drug, whereas 60% of the dose is excreted as metabolites. The remainder is excreted either as unidentified or as unextractable metabolites. The mean terminal plasma elimination half-lives of racemic tramadol and racemic M1 after administration of ULTRAM ER are approximately 7.9 and 8.8 hours, respectively.

Special Populations

Renal

Impaired renal function results in a decreased rate and extent of excretion of tramadol and its active metabolite, M1. The pharmacokinetics of tramadol were studied in patients with mild or moderate renal impairment after receiving multiple doses of ULTRAM ER 100 mg. There is no consistent trend observed for tramadol exposure related to renal function in patients with mild (CLcr: 50-80 mL/min) or moderate (CLcr: 30-50 mL/min) renal impairment in comparison to patients with normal renal function. However, exposure of M1 increased 20-40% with increased severity of the renal impairment (from normal to mild and moderate). ULTRAM ER has not been studied in patients with severe renal impairment (CLcr < 30 mL/min). The limited availability of dose strengths of ULTRAM ER does not permit the dosing flexibility required for safe use in patients with severe renal impairment. Therefore, ULTRAM ER should not be used in patients with severe renal impairment (see PRECAUTIONS, Use in Renal and Hepatic Disease and DOSAGE AND ADMINISTRATION). The total amount of tramadol and M1 removed during a 4-hour dialysis period is less than 7% of the administered dose.

Hepatic

Pharmacokinetics of tramadol was studied in patients with mild or moderate hepatic impairment after receiving multiple doses of ULTRAM ER 100 mg. The exposure of (+)- and (-)-tramadol was similar in mild and moderate hepatic impairment patients in comparison to patients with normal hepatic function. However, exposure of (+)- and (-)-M1 decreased ~50% with increased severity of the hepatic impairment (from normal to mild and moderate). The pharmacokinetics of tramadol after the administration of ULTRAM ER has not been studied in patients with severe hepatic impairment. After the administration of tramadol immediate-release tablets to patients with advanced cirrhosis of the liver, tramadol area under the plasma concentration time curve was larger and the tramadol and M1 half-lives were longer than subjects with normal hepatic function. The limited availability of dose strengths of ULTRAM ER does not permit the dosing flexibility required for safe use in patients with severe hepatic impairment. Therefore, ULTRAM ER should not be used in patients with severe hepatic impairment (see PRECAUTIONS, Use in Renal and Hepatic Disease and DOSAGE AND ADMINISTRATION).

Geriatric

The effect of age on the absorption of tramadol from ULTRAM ER in patients over the age of 65 years has not been studied and is unknown (see PRECAUTIONS and DOSAGE AND ADMINISTRATION).

Gender

Based on pooled multiple-dose pharmacokinetics studies for ULTRAM ER in 166 healthy subjects (111 males and 55 females), the dose-normalized AUC values for tramadol were somewhat higher in females than in males. There was a considerable degree of overlap in values between male and female groups. Dosage adjustment based on gender is not recommended.

Drug Interactions

The formation of the active metabolite, M1, is mediated by CYP2D6. Approximately 7% of the population has reduced activity of the CYP2D6 isoenzyme of cytochrome P-450. Based on a population PK analysis of Phase I studies with immediate-release tablets in healthy subjects, concentrations of tramadol were approximately 20% higher in "poor metabolizers" versus "extensive metabolizers," while M1 concentrations were 40% lower. In vitro drug interaction studies in human liver microsomes indicate that inhibitors of CYP2D6 (fluoxetine, norfluoxetine, amitriptyline, and quinidine) inhibit the metabolism of tramadol to various degrees, suggesting that concomitant administration of these compounds could result in increases in tramadol concentrations and decreased concentrations of M1. The full pharmacological impact of these alterations in terms of either efficacy or safety is unknown.

Tramadol is also metabolized by CYP3A4. Administration of CYP3A4 inhibitors, such as ketoconazole and erythromycin, or inducers, such as rifampin and St. John's Wort, with ULTRAM ER may affect the metabolism of tramadol leading to altered tramadol exposure (see PRECAUTIONS, Drug Interactions).

Quinidine

Tramadol is metabolized to M1 by CYP2D6. A study was conducted to examine the effect of quinidine, a selective inhibitor of CYP2D6, on the pharmacokinetics of tramadol by administering 200 mg quinidine two hours before the administration of ULTRAM ER 100 mg. The results demonstrated that the exposure of tramadol increased 50-60% and the exposure of M1 decreased 50-60% (see PRECAUTIONS, Drug Interactions). In vitro drug interaction studies in human liver microsomes indicate that tramadol has no effect on quinidine metabolism.

Carbamazepine

Carbamazepine, a CYP3A4 inducer, increases tramadol metabolism. Patients taking carbamazepine may have a significantly reduced analgesic effect of tramadol. Because of the seizure risk associated with tramadol, concomitant administration of ULTRAM ER and carbamazepine is not recommended (see PRECAUTIONS, Drug Interactions).

Cimetidine

Concomitant administration of tramadol immediate-release tablets with cimetidine does not result in clinically significant changes in tramadol pharmacokinetics. No alteration of the ULTRAM ER dosage regimen with cimetidine is recommended.

CLINICAL STUDIES

ULTRAM ER was studied in patients with chronic, moderate to moderately severe pain due to osteoarthritis and/or low back pain in four 12-week, randomized, double-blind, placebo-controlled trials. To qualify for inclusion into these studies, patients were required to have moderate to moderately severe pain as defined by a pain intensity score of ≥40 mm, off previous medications, on a 0 – 100 mm visual analog scale (VAS). Adequate evidence of efficacy was demonstrated in the following two studies:

In one 12-week randomized, double-blind, placebo-controlled study, patients with moderate to moderately severe pain due to osteoarthritis of the knee and/or hip were administered doses from 100 mg to 400 mg daily. Treatment was initiated at 100 mg QD for four days then increased by 100 mg per day increments every five days to the randomized fixed dose. Between 51% and 59% of patients in the ULTRAM ER treatment groups completed the study and 56% of patients in the placebo group completed the study. Discontinuations due to adverse events were more common in the ULTRAM ER 200 mg, 300 mg and 400 mg treatment groups (20%, 27%, and 30% of discontinuations, respectively) compared to 14% of the patients treated with ULTRAM ER 100 mg and 20% of patients treated with placebo.

Pain, as assessed by the WOMAC Pain subscale, was measured at 1, 2, 3, 6, 9, and 12 weeks and change from baseline assessed. A responder analysis based on the percent change in WOMAC Pain subscale demonstrated a statistically significant improvement in pain for the 100 mg and 200 mg treatment groups compared to placebo (see Figure 3).

Figure 3

In one 12-week randomized, double-blind, placebo-controlled flexible-dosing trial of ULTRAM ER in patients with osteoarthritis of the knee, patients titrated to an average daily ULTRAM ER dose of approximately 270 mg/day. Forty-nine percent of patients randomized to ULTRAM ER completed the study, while 52% of patients randomized to placebo completed the study. Most of the early discontinuations in the ULTRAM ER treatment group were due to adverse events, accounting for 27% of the early discontinuations in contrast to 7% of the discontinuations from the placebo group. Thirty-four percent of the placebo-treated patients discontinued the study due to lack of efficacy compared to 15% of ULTRAM ER-treated patients. The ULTRAM ER group demonstrated a statistically significant decrease in the mean VAS score, and a statistically significant difference in the responder rate, based on the percent change from baseline in the VAS score, measured at 1, 2, 4, 8, and 12 weeks, between patients receiving ULTRAM ER and placebo (see Figure 4).

Figure 4

INDICATIONS AND USAGE

ULTRAM ER is indicated for the management of moderate to moderately severe chronic pain in adults who require around-the-clock treatment of their pain for an extended period of time.

CONTRAINDICATIONS

ULTRAM ER should not be administered to patients who have previously demonstrated hypersensitivity to tramadol, any other component of this product or opioids. ULTRAM ER is contraindicated in any situation where opioids are contraindicated, including acute intoxication with any of the following: alcohol, hypnotics, narcotics, centrally acting analgesics, opioids or psychotropic drugs. ULTRAM ER may worsen central nervous system and respiratory depression in these patients.

WARNINGS

Seizure Risk

Seizures have been reported in patients receiving tramadol within the recommended dosage range. Spontaneous post-marketing reports indicate that seizure risk is increased with doses of tramadol above the recommended range. Concomitant use of tramadol increases the seizure risk in patients taking:

- Selective serotonin re-uptake inhibitors (SSRI antidepressants or anorectics),
- Tricyclic antidepressants (TCAs), and other tricyclic compounds (e.g., cyclobenzaprine, promethazine, etc.), or
- Other opioids.

Administration of tramadol may enhance the seizure risk in patients taking:

- MAO inhibitors (see also WARNINGS, Use with MAO Inhibitors),
- Neuroleptics, or
- Other drugs that reduce the seizure threshold.

Risk of convulsions may also increase in patients with epilepsy, those with a history of seizures, or in patients with a recognized risk for seizure (such as head trauma, metabolic disorders, alcohol and drug withdrawal, CNS infections). In tramadol overdose, naloxone administration may increase the risk of seizure.

Suicide Risk

- Do not prescribe ULTRAM ER for patients who are suicidal or addiction-prone.
- Prescribe ULTRAM ER with caution for patients taking tranquilizers or antidepressant drugs and patients who use alcohol in excess.
- Tell your patients not to exceed the recommended dose and to limit their intake of alcohol.

Serotonin Syndrome Risk

The development of a potentially life-threatening serotonin syndrome may occur with the use of tramadol products, including ULTRAM ER, particularly with concomitant use of serotonergic drugs such as SSRIs, SNRIs, TCAs, MAOIs and triptans, with drugs which impair metabolism of serotonin (including MAOIs), and with drugs which impair metabolism of tramadol (CYP2D6 and CYP3A4 inhibitors). This may occur within the recommended dose. (see CLINICAL PHARMACOLOGY, Pharmacokinetics).

Serotonin syndrome may include mental-status changes (e.g., agitation, hallucinations, coma), autonomic instability (e.g., tachycardia, labile blood pressure, hyperthermia), neuromuscular aberrations (e.g., hyperreflexia, incoordination) and/or gastrointestinal symptoms (e.g., nausea, vomiting, diarrhea).

Tramadol products in excessive doses, either alone or in combination with other CNS depressants, including alcohol, are a major cause of drug-related deaths. Fatalities within the first hour of overdosage are not uncommon. Tramadol should not be taken in doses higher than those recommended by the physician. The judicious prescribing of tramadol is essential to the safe use of this drug. With patients who are depressed or suicidal, consideration should be given to the use of non-narcotic analgesics. Patients should be cautioned about the concomitant use of tramadol products and alcohol because of potentially serious CNS-additive effects of these agents. Because of its added depressant effects, tramadol should be prescribed with caution for those patients whose medical condition requires the concomitant administration of sedatives, tranquilizers, muscle relaxants, antidepressants, or other CNS-depressant drugs. Patients should be advised of the additive depressant effects of these combinations.

Many of the tramadol-related deaths have occurred in patients with previous histories of emotional disturbances or suicidal ideation or attempts as well as histories of misuse of tranquilizers, alcohol, and other CNS-active drugs. Some deaths have occurred as a consequence of the accidental ingestion of excessive quantities of tramadol alone or in combination with other drugs. Patients taking tramadol should be warned not to exceed the dose recommended by their physician.

Anaphylactoid Reactions

Serious and rarely fatal anaphylactoid reactions have been reported in patients receiving therapy with tramadol. When these events do occur it is often following the first dose. Other reported allergic reactions include pruritus, hives, bronchospasm, angioedema, toxic epidermal necrolysis and Stevens-Johnson syndrome. Patients with a history of anaphylactoid reactions to codeine and other opioids may be at increased risk and therefore should not receive ULTRAM ER (see CONTRAINDICATIONS).

Respiratory Depression

Administer ULTRAM ER cautiously in patients at risk for respiratory depression. In these patients alternative non-opioid analgesics should be considered. When large doses of tramadol are administered with anesthetic medications or alcohol, respiratory depression may result. Respiratory depression should be treated as an overdose. If naloxone is to be administered, use cautiously because it may precipitate seizures (see WARNINGS, Seizure Risk and OVERDOSAGE).

Interaction With Central Nervous System (CNS) Depressants

ULTRAM ER should be used with caution and in reduced dosages when administered to patients receiving CNS depressants such as alcohol, opioids, anesthetic agents, narcotics, phenothiazines, tranquilizers or sedative hypnotics. ULTRAM ER increases the risk of CNS and respiratory depression in these patients.

Increased Intracranial Pressure or Head Trauma

ULTRAM ER should be used with caution in patients with increased intracranial pressure or head injury. The respiratory depressant effects of opioids include carbon dioxide retention and secondary elevation of cerebrospinal fluid pressure, and may be markedly exaggerated in these patients. Additionally, pupillary changes (miosis) from tramadol may obscure the existence, extent, or course of intracranial pathology. Clinicians should also maintain a high index of suspicion for adverse drug reaction when evaluating altered mental status in these patients if they are receiving ULTRAM ER. (see WARNINGS, Respiratory Depression.)

Use in Ambulatory Patients

ULTRAM ER may impair the mental and or physical abilities required for the performance of potentially hazardous tasks such as driving a car or operating machinery. The patient using this drug should be cautioned accordingly.

Use With MAO Inhibitors and Serotonin Re-uptake Inhibitors

Use ULTRAM ER with great caution in patients taking monoamine oxidase inhibitors. Animal studies have shown increased deaths with combined administration. Concomitant use of ULTRAM ER with MAO inhibitors or SSRIs increases the risk of adverse events, including seizure and serotonin syndrome.

Withdrawal

Withdrawal symptoms may occur if ULTRAM ER is discontinued abruptly. These symptoms may include: anxiety, sweating, insomnia, rigors, pain, nausea, tremors, diarrhea, upper respiratory symptoms, piloerection, and rarely hallucinations. Clinical experience suggests that withdrawal symptoms may be reduced by tapering ULTRAM ER.

Misuse, Abuse and Diversion of Opioids

Tramadol is an opioid agonist of the morphine-type. Such drugs are sought by drug abusers and people with addiction disorders and are subject to criminal diversion.

Tramadol can be abused in a manner similar to other opioid agonists, legal or illicit. This should be considered when prescribing or dispensing ULTRAM ER in situations where the physician or pharmacist is concerned about an increased risk of misuse, abuse, or diversion.

ULTRAM ER could be abused by crushing, chewing, snorting, or injecting the dissolved product. These practices will result in the uncontrolled delivery of the opioid and pose a significant risk to the abuser that could result in overdose and death (see WARNINGS and DRUG ABUSE AND ADDICTION).

Concerns about abuse, addiction, and diversion should not prevent the proper management of pain. The development of addiction to opioid analgesics in properly managed patients with pain has been reported to be rare. However, data are not available to establish the true incidence of addiction in chronic pain patients.

Healthcare professionals should contact their State Professional Licensing Board or State Controlled Substances Authority for information on how to prevent and detect abuse or diversion of this product.

Interactions with Alcohol and Drugs of Abuse

Tramadol may be expected to have additive effects when used in conjunction with alcohol, other opioids, or illicit drugs that cause central nervous system depression.

DRUG ABUSE AND ADDICTION

ULTRAM® ER is a mu-agonist opioid. Tramadol, like other opioids used in analgesia, can be abused and is subject to criminal diversion.

Drug addiction is characterized by compulsive use, use for non-medical purposes, and continued use despite harm or risk of harm. Drug addiction is a treatable disease, utilizing a multi-disciplinary approach, but relapse is common.

"Drug-seeking" behavior is very common in addicts and drug abusers. Drug-seeking tactics include emergency calls or visits near the end of office hours, refusal to undergo appropriate examination, testing or referral, repeated "loss" of prescriptions, tampering with prescriptions and reluctance to provide prior medical records or contact information for other treating physician(s). "Doctor shopping" to obtain additional prescriptions is common among drug abusers and people suffering from untreated addiction.

Abuse and addiction are separate and distinct from physical dependence and tolerance. Physicians should be aware that addiction may not be accompanied by concurrent tolerance and symptoms of physical dependence in all addicts. In addition, abuse of opioids can occur in the absence of true addiction and is characterized by misuse for non-medical purposes, often in combination with other psychoactive substances. ULTRAM ER, like other opioids, may be diverted for non-medical use. Careful record-keeping of prescribing information, including quantity, frequency, and renewal requests is strongly advised.

Proper assessment of the patient, proper prescribing practices, periodic re-evaluation of therapy, and proper dispensing and storage are appropriate measures that help to limit abuse of opioid drugs.

ULTRAM ER is intended for oral use only. The crushed tablet poses a hazard of overdose and death. This risk is increased with concurrent abuse of alcohol and other substances. With parenteral abuse, the tablet excipients can be expected to result in local tissue necrosis, infection, pulmonary granulomas, and increased risk of endocarditis and valvular heart injury. Parenteral drug abuse is commonly associated with transmission of infectious diseases such as hepatitis and HIV.

Risk of Overdosage

Serious potential consequences of overdosage with ULTRAM ER are central nervous system depression, respiratory depression and death. In treating an overdose, primary attention should be given to maintaining adequate ventilation along with general supportive treatment (see OVERDOSAGE).

PRECAUTIONS

Acute Abdominal Condition

The administration of ULTRAM ER may complicate the clinical assessment of patients with acute abdominal conditions.

Use in Renal and Hepatic Disease

Impaired renal function results in a decreased rate and extent of excretion of tramadol and its active metabolite, M1. ULTRAM ER has not been studied in patients with severe renal impairment (CLcr < 30 mL/min). The limited availability of dose strengths and once daily dosing of ULTRAM ER do not permit the dosing flexibility required for safe use in patients with severe renal impairment. Therefore, ULTRAM ER should not be used in patients with severe renal impairment (see CLINICAL PHARMACOLOGY and DOSAGE AND ADMINISTRATION). Metabolism of tramadol and M1 is reduced in patients with advanced cirrhosis of the liver. The pharmacokinetics of ULTRAM ER has not been studied in patients with severe hepatic impairment. The limited availability of dose strengths and once daily dosing of ULTRAM ER do not permit the dosing flexibility required for safe use in patients with severe hepatic impairment. Therefore, ULTRAM ER should not be used in patients with severe hepatic impairment (see CLINICAL PHARMACOLOGY and DOSAGE AND ADMINISTRATION).

INFORMATION FOR PATIENTS

- Patients should be informed that ULTRAM ER is for oral use only and should be swallowed whole. The tablets should not be chewed, crushed, or split.
- Patients should be informed that ULTRAM ER may cause seizures and/or serotonin syndrome with concomitant use of serotonergic agents (including SSRIs, SNRIs, and triptans) or drugs that significantly reduce the metabolic clearance of tramadol.
- Patients should be informed that ULTRAM ER may impair mental or physical abilities required for the performance of potentially hazardous tasks such as driving a car or operating machinery.
- Patients should be informed that ULTRAM ER should not be taken with alcohol containing beverages.
- Patients should be informed that ULTRAM ER should be used with caution when taking medications such as tranquilizers, hypnotics or other opiate containing analgesics.
- Female patients should be instructed to inform the prescriber if they are pregnant, think they might become pregnant, or are trying to become pregnant (see PRECAUTIONS, Labor and Delivery).
- Patients should be educated regarding the single-dose and 24-hour dosing regimen, as exceeding these recommendations can result in respiratory depression, seizures or death.

Use in Drug and Alcohol Addiction

ULTRAM ER is an opioid with no approved use in the management of addictive disorders. Its proper usage in individuals with drug or alcohol dependence, either active or in remission, is for the management of pain requiring opioid analgesia.

Drug Interactions

CYP2D6 and CYP3A4 inhibitors: Concomitant administration of CYP2D6 and/or CYP3A4 inhibitors (see CLINICAL PHARMACOLOGY, Pharmacokinetics), such as quinidine, fluoxetine, paroxetine and amitriptyline (CYP2D6 inhibitors), and ketoconazole and erythromycin (CYP3A4 inhibitors), may reduce metabolic clearance of tramadol increasing the risk for serious adverse events including seizures and serotonin syndrome.

Serotonergic Drugs: There have been postmarketing reports of serotonin syndrome with use of tramadol and SSRIs/SNRIs or MAOIs and α2-adrenergic blockers. Caution is advised when ULTRAM ER is coadministered with other drugs that may affect the serotonergic neurotransmitter systems, such as SSRIs, MAOIs, triptans, linezolid (an antibiotic which is a reversible non-selective MAOI), lithium, or St. John's Wort. If concomitant treatment of ULTRAM ER with a drug affecting the serotonergic neurotransmitter system is clinically warranted, careful observation of the patient is advised, particularly during treatment initiation and dose increases (see Warnings, Serotonin Syndrome Risk).

Triptans: Based on the mechanism of action of tramadol and the potential for serotonin syndrome, caution is advised when ULTRAM ER is coadministered with a triptan. If concomitant treatment of ULTRAM ER with a triptan is clinically warranted, careful observation of the patient is advised, particularly during treatment initiation and dose increases (see WARNINGS, Serotonin Syndrome Risk).

Use With Carbamazepine

Patients taking carbamazepine, a CYP3A4 inducer, may have a significantly reduced analgesic effect of tramadol. Because carbamazepine increases tramadol metabolism and because of the seizure risk associated with tramadol, concomitant administration of ULTRAM ER and carbamazepine is not recommended.

Use With Quinidine

Coadministration of quinidine with ULTRAM ER resulted in a 50-60% increase in tramadol exposure and a 50-60% decrease in M1 exposure (see CLINICAL PHARMACOLOGY, Drug Interactions). The clinical consequences of these findings are unknown.

Use With Digoxin and Warfarin

Post-marketing surveillance of tramadol has revealed rare reports of digoxin toxicity and alteration of warfarin effect, including elevation of prothrombin times.

Potential for Other Drugs to Affect Tramadol

In vitro drug interaction studies in human liver microsomes indicate that concomitant administration with inhibitors of CYP2D6 such as fluoxetine, paroxetine, and amitriptyline could result in some inhibition of the metabolism of tramadol.

Administration of CYP3A4 inhibitors, such as ketoconazole and erythromycin, or inducers, such as rifampin and St. John's Wort, with ULTRAM ER may affect the metabolism of tramadol leading to altered tramadol exposure.

Potential for Tramadol to Affect Other Drugs

In vitro drug interaction studies in human liver microsomes indicate that tramadol has no effect on quinidine metabolism. In vitro studies indicate that tramadol is unlikely to inhibit the CYP3A4-mediated metabolism of other drugs when administered concomitantly at therapeutic doses. Tramadol is a mild inducer of selected drug metabolism pathways measured in animals.

CARCINOGENESIS, MUTAGENESIS, IMPAIRMENT OF FERTILITY

No carcinogenic effect of tramadol was observed in p53(+/–)-heterozygous mice at oral doses up to 150 mg/kg/day (approximately 2-fold maximum daily human dose [MDHD] of 400 mg/day for a 60 kg adult based on body surface conversion) for 26 weeks and in rats at oral doses up to 75 mg/kg/day for males and 100 mg/kg/day for females (approximately 2-fold MDHD) for two years. However, the excessive decrease in body weight gain observed in the rat study might have reduced their sensitivity to any potential carcinogenic effect of the drug.

Tramadol was not mutagenic in the following assays: a bacterial reverse mutation assay using Salmonella and E. coli, a mouse lymphoma assay (in the absence of metabolic activation), and a bone marrow micronucleus test in mice. Mutagenic results occurred in the presence of metabolic activation in the mouse lymphoma assay. Overall, the weight of evidence from these tests indicates that tramadol does not pose a genotoxic risk to humans.

No effects on fertility were observed for tramadol at oral dose levels up to 50 mg/kg/day in male and female rats (approximately equivalent to MDHD).

Pregnancy

Teratogenic Effects: Pregnancy Category C

Tramadol was not teratogenic at oral dose levels up to 50 mg/kg/day (approximately equivalent to MDHD) in rats and 100 mg/kg (approximately 5-fold MDHD) in rabbits during organogenesis. However, embryo-fetal lethality, reductions in fetal weight and skeletal ossification, and increased supernumerary ribs were observed at a maternal toxic dose of 140 mg/kg in mice (approximately 2-fold MDHD), 80 mg/kg in rats (2-fold MDHD) or 300 mg/kg in rabbits (approximately 15-fold MDHD).

Non-teratogenic Effects

Tramadol caused a reduction in neonatal body weight and survival at an oral dose of 80 mg/kg (approximately 2-fold MDHD) when rats were treated during late gestation throughout lactation period.

There are no adequate and well-controlled studies in pregnant women. ULTRAM ER should be used during pregnancy only if the potential benefit justifies the potential risk to the fetus. Neonatal seizures, neonatal withdrawal syndrome, fetal death and still birth have been reported during post-marketing reports with tramadol HCl immediate-release products.

Labor and Delivery

ULTRAM ER should not be used in pregnant women prior to or during labor unless the potential benefits outweigh the risks. Safe use in pregnancy has not been established. Chronic use during pregnancy may lead to physical dependence and post-partum withdrawal symptoms in the newborn (see DRUG ABUSE AND ADDICTION). Tramadol has been shown to cross the placenta. The mean ratio of serum tramadol in the umbilical veins compared to maternal veins was 0.83 for 40 women treated with tramadol HCl during labor.

The effect of ULTRAM ER, if any, on the later growth, development, and functional maturation of the child is unknown.

Nursing Mothers

ULTRAM ER is not recommended for obstetrical preoperative medication or for post-delivery analgesia in nursing mothers because its safety in infants and newborns has not been studied. Following a single IV 100-mg dose of tramadol, the cumulative excretion in breast milk within sixteen hours postdose was 100 µg of tramadol (0.1% of the maternal dose) and 27 µg of M1.

Pediatric Use

The safety and efficacy of ULTRAM ER in patients under 18 years of age have not been established. The use of ULTRAM ER in the pediatric population is not recommended.

Geriatric Use

Nine-hundred-one elderly (65 years of age or older) subjects were exposed to ULTRAM ER in clinical trials. Of those subjects, 156 were 75 years of age and older. In general, higher incidence rates of adverse events were observed for patients older than 65 years of age compared with patients 65 years and younger, particularly for the following adverse events: constipation, fatigue, weakness, postural hypotension and dyspepsia. For this reason, ULTRAM ER should be used with great caution in patients older than 75 years of age (see CLINICAL PHARMACOLOGY and DOSAGE AND ADMINISTRATION).

ADVERSE REACTIONS

ULTRAM ER was administered to a total of 3108 patients during studies conducted in the U.S. These included four double-blind studies in patients with osteoarthritis and/or chronic low back pain and one open-label study in patients with chronic non-malignant pain. A total of 901 patients were 65 years or older. The frequency of adverse events generally^7 increased with doses from 100 mg to 400 mg in the two pooled, twelve-week, randomized, double-blind, placebo-controlled studies in patients with chronic non-malignant pain (see Table 2).

Table 2: Incidence (%) of patients with adverse event rates ≥ 5% from two 12-week placebo-controlled studies in patients with moderate to moderately severe chronic pain by dose (N=1811).
 | ULTRAM ER |  |  |  | Placebo
MedDRA Preferred Term | 100 mg (N=403) n (%) | 200 mg (N=400) n (%) | 300 mg (N=400) n (%) | 400 mg (N=202) n (%) | (N=406) n (%)
Dizziness (not vertigo) | 64 (15.9) | 81 (20.3) | 90 (22.5) | 57 (28.2) | 28 (6.9)
Nausea | 61 (15.1) | 90 (22.5) | 102 (25.5) | 53 (26.2) | 32 (7.9)
Constipation | 49 (12.2) | 68 (17.0) | 85 (21.3) | 60 (29.7) | 17 (4.2)
Headache | 49 (12.2) | 62 (15.5) | 46 (11.5) | 32 (15.8) | 43 (10.6)
Somnolence | 33 (8.2) | 45 (11.3) | 29 (7.3) | 41 (20.3) | 7 (1.7)
Flushing | 31 (7.7) | 40 (10.0) | 35 (8.8) | 32 (15.8) | 18 (4.4)
Pruritus | 25 (6.2) | 34 (8.5) | 30 (7.5) | 24 (11.9) | 4 (1.0)
Vomiting | 20 (5.0) | 29 (7.3) | 34 (8.5) | 19 (9.4) | 11 (2.7)
Insomnia | 26 (6.5) | 32 (8.0) | 36 (9.0) | 22 (10.9) | 13 (3.2)
Dry Mouth | 20 (5.0) | 29 (7.3) | 39 (9.8) | 18 (8.9) | 6 (1.5)
Diarrhea | 15 (3.7) | 27 (6.8) | 37 (8.5) | 10 (5.0) | 17 (4.2)
Asthenia | 14 (3.5) | 24 (6.0) | 26 (6.5) | 13 (6.4) | 7 (1.7)
Postural hypotension | 7 (1.7) | 17 (4.3) | 8 (2.0) | 11 (5.4) | 9 (2.2)
Sweating increased | 6 (1.5) | 8 (2.0) | 15 (3.8) | 13 (6.4) | 1 (0.2)
Anorexia | 3 (0.7) | 7 (1.8) | 21 (5.3) | 12 (5.9) | 1 (0.2)

The following adverse events were reported from all the chronic pain studies (N=3108).

The lists below include adverse events not otherwise noted in Table 2.

Adverse events with incidence rates of 1.0% to <5.0%

Eye disorders: vision blurred

Gastrointestinal disorders: abdominal pain upper, dyspepsia, abdominal pain, sore throat

General disorders: weakness, pain, feeling hot, influenza like illness, fall, rigors, lethargy, pyrexia, chest pain

Infections and infestations: nasopharyngitis, upper respiratory tract infection, sinusitis, influenza, gastroenteritis viral, urinary tract infection, bronchitis

Investigations: blood creatine phosphokinase increased, weight decreased

Metabolism and nutrition disorders: appetite decreased

Musculoskeletal, connective tissue and bone disorders: arthralgia, back pain, pain in limb, neck pain

Nervous system disorders: tremor, paresthesia, hypoesthesia

Psychiatric disorders: nervousness, anxiety, depression, restlessness

Respiratory, thoracic and mediastinal disorders: sneezing, cough, rhinorrhea, nasal congestion, dyspnea, sinus congestion

Skin and subcutaneous tissue disorders: sweating increased, dermatitis

Vascular disorders: hot flushes, vasodilatation

Adverse events with incidence rates of 0.5% to <1.0% and serious adverse events reported in at least 2 patients.

Cardiac disorders: palpitations, myocardial infarction

Ear and labyrinth disorders: tinnitus, vertigo

Gastrointestinal disorders: flatulence, toothache, constipation aggravated, appendicitis, pancreatitis

General disorders: feeling jittery, edema lower limb, shivering, joint swelling, malaise, drug withdrawal syndrome, peripheral swelling

Hepato-biliary disorders: cholelithiasis, cholecystitis

Infections and infestations: cellulitis, ear infection, gastroenteritis, pneumonia, viral infection

Injury and poisoning: joint sprain, muscle injury

Investigations: alanine aminotransferase increased, blood pressure increased, aspartate aminotransferase increased, heart rate increased, blood glucose increased, liver function tests abnormal ,

Musculoskeletal, connective tissue and bone disorders: muscle cramps, muscle spasms, joint stiffness, muscle twitching, myalgia, osteoarthritis aggravated

Nervous system disorders: migraine, sedation, syncope, disturbance in attention, dizziness aggravated

Psychiatric disorders: euphoric mood, irritability, libido decreased, sleep disorder, agitation, disorientation, abnormal dreams

Renal and urinary disorders: difficulty in micturition, urinary frequency, hematuria, dysuria, urinary retention

Respiratory, thoracic and mediastinal disorders: yawning

Skin and subcutaneous tissue disorders: contusion, piloerection, clamminess, night sweats, urticaria

Vascular disorders: hypertension aggravated, hypertension, peripheral ischemia

OVERDOSAGE

Acute overdosage with tramadol can be manifested by respiratory depression, somnolence progressing to stupor or coma, skeletal muscle flaccidity, cold and clammy skin, constricted pupils, bradycardia, hypotension, and death.

Deaths due to overdose have been reported with abuse and misuse of tramadol by ingesting, inhaling, or injecting the crushed tablets. Review of case reports has indicated that the risk of fatal overdose is further increased when tramadol is abused concurrently with alcohol or other CNS depressants, including other opioids.

In the treatment of tramadol overdosage, primary attention should be given to the re-establishment of a patent airway and institution of assisted or controlled ventilation. Supportive measures (including oxygen and vasopressors) should be employed in the management of circulatory shock and pulmonary edema accompanying overdose as indicated. Cardiac arrest or arrhythmias may require cardiac massage or defibrillation.

While naloxone will reverse some, but not all, symptoms caused by overdosage with tramadol, the risk of seizures is also increased with naloxone administration. In animals convulsions following the administration of toxic doses of ULTRAM ER could be suppressed with barbiturates or benzodiazepines but were increased with naloxone. Naloxone administration did not change the lethality of an overdose in mice. Hemodialysis is not expected to be helpful in an overdose because it removes less than 7% of the administered dose in a 4-hour dialysis period.

DOSAGE AND ADMINISTRATION

ULTRAM ER should not be used in patients with:

- creatinine clearance less than 30 mL/min,
- severe hepatic impairment (Child-Pugh Class C)

(See PRECAUTIONS, Use in Renal and Hepatic Disease).

ULTRAM ER must be swallowed whole and must not be chewed, crushed, or split (see WARNINGS, Misuse, Abuse and Diversion of Opioids and DRUG ABUSE AND ADDICTION).

Adults (18 years of age and over)

Patients Not Currently on Tramadol Immediate-Release Products

For patients not currently treated with tramadol immediate-release (IR) products, ULTRAM ER should be initiated at a dose of 100 mg once daily and titrated up as necessary by 100-mg increments every five days to relief of pain and depending upon tolerability. ULTRAM ER should not be administered at a dose exceeding 300 mg per day.

Patients Currently on Tramadol Immediate-Release Products

For patients maintained on tramadol IR products, calculate the 24-hour tramadol IR dose and initiate a total daily dose of ULTRAM ER rounded down to the next lowest 100 mg increment. The dose may subsequently be individualized according to patient need. Due to limitations in flexibility of dose selection with ULTRAM ER, some patients maintained on tramadol IR products may not be able to convert to ULTRAM ER. ULTRAM ER should not be administered at a dose exceeding 300 mg per day. The concomitant use of ULTRAM ER with other tramadol products is not recommended (see WARNINGS).

Individualization of Dose

Good pain management practice dictates that the dose be individualized according to patient need using the lowest beneficial dose. Start at the lowest possible dose and titrate upward as tolerated to achieve an adequate effect. Clinical studies of ULTRAM ER have not demonstrated a clinical benefit at a total daily dose exceeding 300 mg.

In general, dosing of an elderly patient (over 65 years of age) should be initiated cautiously, usually starting at the low end of the dosing range, reflecting the greater frequency of decreased hepatic, renal or cardiac function and of concomitant disease or other drug therapy. ULTRAM ER should be administered with even greater caution in patients over 75 years, due to the greater frequency of adverse events seen in this population.

HOW SUPPLIED

ULTRAM ER (tramadol hydrochloride) Extended-release tablets are supplied in the following package and dose strength forms:

100 mg: Round, convex, white to off-white tablets imprinted with "100" over "ER" on one side in black ink

Bottle of 30 tablets – NDC 21695-292-30

200 mg: Round, convex, white to off-white tablets imprinted with "200" over "ER" on one side in black ink

Bottle of 30 tablets – NDC 21695-563-30

300 mg: Round, convex, white to off-white tablets imprinted with "300" over "ER" on one side in black ink

Bottle of 30 tablets – NDC 21695-913-30

Store at 25°C (77°F); excursions permitted to 15-30°C (59 - 86°F).

Manufactured by:
Biovail Corporation, Mississauga, ON L5N 8M5, Canada

Made in Canada

Distributed by:
PriCara, a unit of Ortho-McNeil, Inc., Raritan, NJ 08869

Repackaged by:

Rebel Distributors Corp

Thousand Oaks, CA 91320